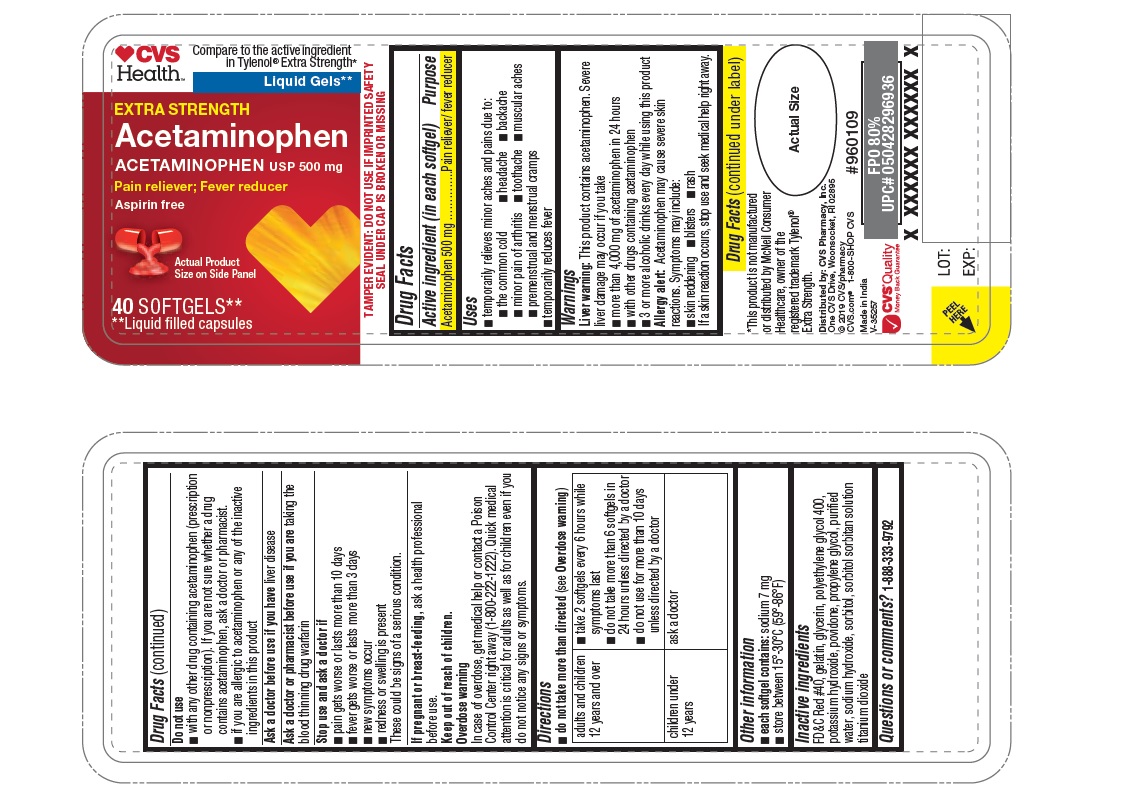 DRUG LABEL: CVS Health Extra Strength Acetaminophen Softgels
NDC: 69842-636 | Form: CAPSULE, LIQUID FILLED
Manufacturer: CVS Pharrmacy
Category: otc | Type: HUMAN OTC DRUG LABEL
Date: 20241217

ACTIVE INGREDIENTS: ACETAMINOPHEN 500 mg/1 1
INACTIVE INGREDIENTS: GELATIN; GLYCERIN; POLYETHYLENE GLYCOL 400; POTASSIUM HYDROXIDE; POVIDONE K30; PROPYLENE GLYCOL; SODIUM HYDROXIDE; WATER; SORBITAN; SORBITOL; TITANIUM DIOXIDE; FD&C RED NO. 40

CVS Health Extra Strength Aceatminophen Softgels

Drug Facts

Active ingredient (in each softgel)

Acetaminophen 500 mg

Purpose

Pain reliever/ fever reducer

Uses

■ temporarily relieves minor aches and pains due to:
■ the common cold ■ headache ■ backache
■ minor pain of arthritis ■ toothache ■ muscular aches
■ premenstrual and menstrual cramps
■ temporarily reduces fever

Warnings

Liver warning: This product contains acetaminophen. Severe
liver damage may occur if you take
■ more than 4,000 mg of acetaminophen in 24 hours
■ with other drugs containing acetaminophen
■ 3 or more alcoholic drinks every day while using this product
Allergy alert: Acetaminophen may cause severe skin
reactions. Symptoms may include:
■ skin reddening ■ blisters ■ rash
If a skin reaction occurs, stop use and seek medical help right away.

Do not use

■ with any other drug containing acetaminophen (prescription
or nonprescription). If you are not sure whether a drug
contains acetaminophen, ask a doctor or pharmacist.
■ if you are allergic to acetaminophen or any of the inactive
ingredients in this product

Ask a doctor before use if you have liver disease

Ask a doctor or pharmacist before use if you are taking the blood thinning drug warfarin.

STOP USE

■ pain gets worse or lasts more than 10 days
■ fever gets worse or lasts more than 3 days
■ new symptoms occur
■ redness or swelling is present
These could be signs of a serious condition.

PREGNANCY OR BREAST FEEDING

If pregnant or breast-feeding, ask a health professional before use.

Keep out of reach of children.

Overdose warning

In case of overdose, get medical help or contact a Poison Control Center right away (1-800-222-1222). Quick medical attention is critical for adults as well as for children even if you do not notice any signs or symptoms.

Directions

do not take more than directed (see Overdose warning)

Adults and children 12 years and over | ■ take 2 softgels every 6 hours while symptoms last ■ do not take more than 6 softgels in 24 hours unless directed by a doctor ■ do not use for more than 10 days unless directed by a doctor
children under 12 years | ask a doctor

Other information

■ each softgel contains: sodium 7 mg
■ store between 15°-30°C (59°-86°F)

Inactive ingredients

FD&C Red #40, gelatin, glycerin, polyethylene glycol 400,
potassium hydroxide, povidone, propylene glycol, purified
water, sodium hydroxide, sorbitol, sorbitol sorbitan solution
titanium dioxide

Questions or Comments? 1-888-333-9792

PRINCIPAL DISPLAY PANEL

CVS Health

Compare to the active ingredient
in Tylenol® Extra Strength*
Liquid Gels**

EXTRA STRENGTH
Acetaminophen USP 500mg

Pain Reliever; Fever reducer
Aspirin free
40 SOFTGELS**
**Liquid filled capsules

TAMPER EVIDENT: DO NOT USE IF IMPRINTED SAFETY
SEAL UNDER CAP IS BROKEN OR MISSING

This product is not manufactured
or distributed by McNeil Consumer
Healthcare, owner of the
registered trademark Tylenol®
Extra Strength.

Distributed by: CVS Pharmacy, Inc.
One CVS Drive, Woonsocket, RI 02895
© 2019 CVS/pharmacy
CVS.com® 1-800-SHOP CVS
Made in India
V-35257
#960109